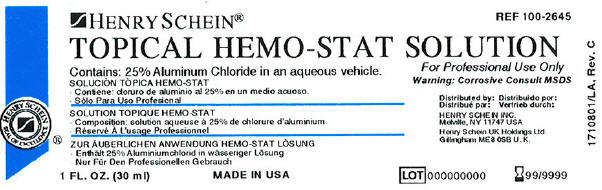 DRUG LABEL: Topical Hemo-Stat
NDC: 0404-1080 | Form: SOLUTION
Manufacturer: Henry Schein
Category: prescription | Type: HUMAN PRESCRIPTION DRUG LABEL
Date: 20100513

ACTIVE INGREDIENTS: Aluminum Chloride 250 mg/1 g
INACTIVE INGREDIENTS: Water

TOPICAL
HEMO-STAT
SOLUTION

DIRECTIONS

Soak a cotton-tipped applicator or a pledget of cotton with Hemo-Stat. Apply to bleeding area with pressure until hemorrhage is arrested.

Note

Should a small dark coagulum appear, flush it away with water. This will have no effect on the hemostatic action.

Hemo-Stat Solution contains 25% Aluminum Chloride in an aqueous vehicle. It contains no epinephrine.

CAUTION

Federal (U.S.A.) Law prohibits dispensing without a prescription.

Made in USA

PRINCIPAL DISPLAY PANEL - 30 ml Bottle Label

HENRY SCHEIN®
TOPICAL HEMO-STAT SOLUTION

REF 100-2645

Contains: 25% Aluminum Chloride in an aqueous vehicle.

For Professional Use Only
Warning: Corrosive Consult MSDS

Distributed by:

HENRY SCHEIN INC.
Melville, NY 11747 USA

Henry Schein U.K. Holdings Ltd.
Gillingham ME 8 0SB U.K.

1 FL. OZ. (30 ml)

MADE IN USA